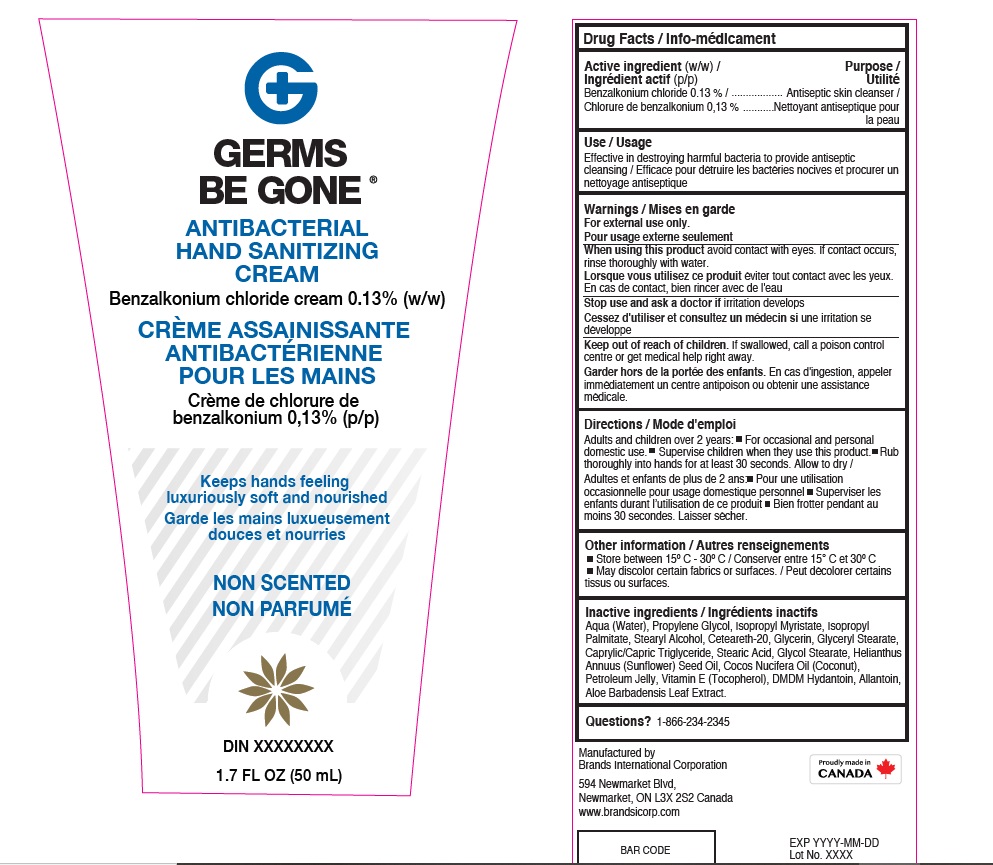 DRUG LABEL: Germs Be Gone Antibacterial
NDC: 50157-523 | Form: CREAM
Manufacturer: BRANDS INTERNATIONAL CORPORATION
Category: otc | Type: HUMAN OTC DRUG LABEL
Date: 20210814

ACTIVE INGREDIENTS: BENZALKONIUM CHLORIDE 0.13 g/100 mL
INACTIVE INGREDIENTS: PHENOXYETHANOL; STEARYL ALCOHOL; POLYOXYL 20 CETOSTEARYL ETHER; GLYCERIN; WATER; STEARIC ACID; SUNFLOWER OIL; COCONUT OIL; PETROLATUM; TRICAPRYLIN; ALLANTOIN; ISOPROPYL MYRISTATE; PROPYLENE GLYCOL; DMDM HYDANTOIN; GLYCERYL MONOSTEARATE; ALPHA-TOCOPHEROL ACETATE; ISOPROPYL PALMITATE

Germs Be Gone Antibacterial Hand Sanitizing cream

Active Ingredient(s)

Benzalkonium chloride 0.05 %.

Purpose

Antiseptic skin cleanser

Use

To help reduce bacteria on hands.

Warnings

For external use only.

Do not use

- in children less than 2 months of age
- on open skin wounds

When using this product keep out of eyes, ears, and mouth. In case of contact with eyes, rinse eyes thoroughly with water.
Stop use and ask a doctor if irritation or rash occurs. These may be signs of a serious condition.
Keep out of reach of children. If swallowed, get medical help or contact a Poison Control Center right away.

Stop use and ask a doctor if irritation or rash occurs. These may be signs of a serious condition.

Keep out of reach of children. If swallowed, get medical help or contact a Poison Control Center right away

Directions

- Rub thoroughly on hands for at least 30 seconds and allow to dry
- Supervise children when using this product to avoid swallowing.
- Adults and children over 2 years
- For occasional and domestic use

Other information

- Store between 15-30C (59-86F)
- May discolor certain fabrics or surfaces

Inactive ingredients

Aqua (Water), Propylene Glycol, Isopropyl Myristate, Isopropyl Palmitate, Stearyl Alcohol, Ceteareth-20, Glycerin, Glyceryl Stearate,
Caprylic/Capric Triglyceride, Stearic Acid, Glycol Stearate, Helianthus Annuus (Sunflower) Seed Oil, Cocos Nucifera Oil (Coconut),
Petroleum Jelly, Vitamin E (Tocopherol), DMDM Hydantoin, Allantoin, Aloe Barbadensis Leaf Extract